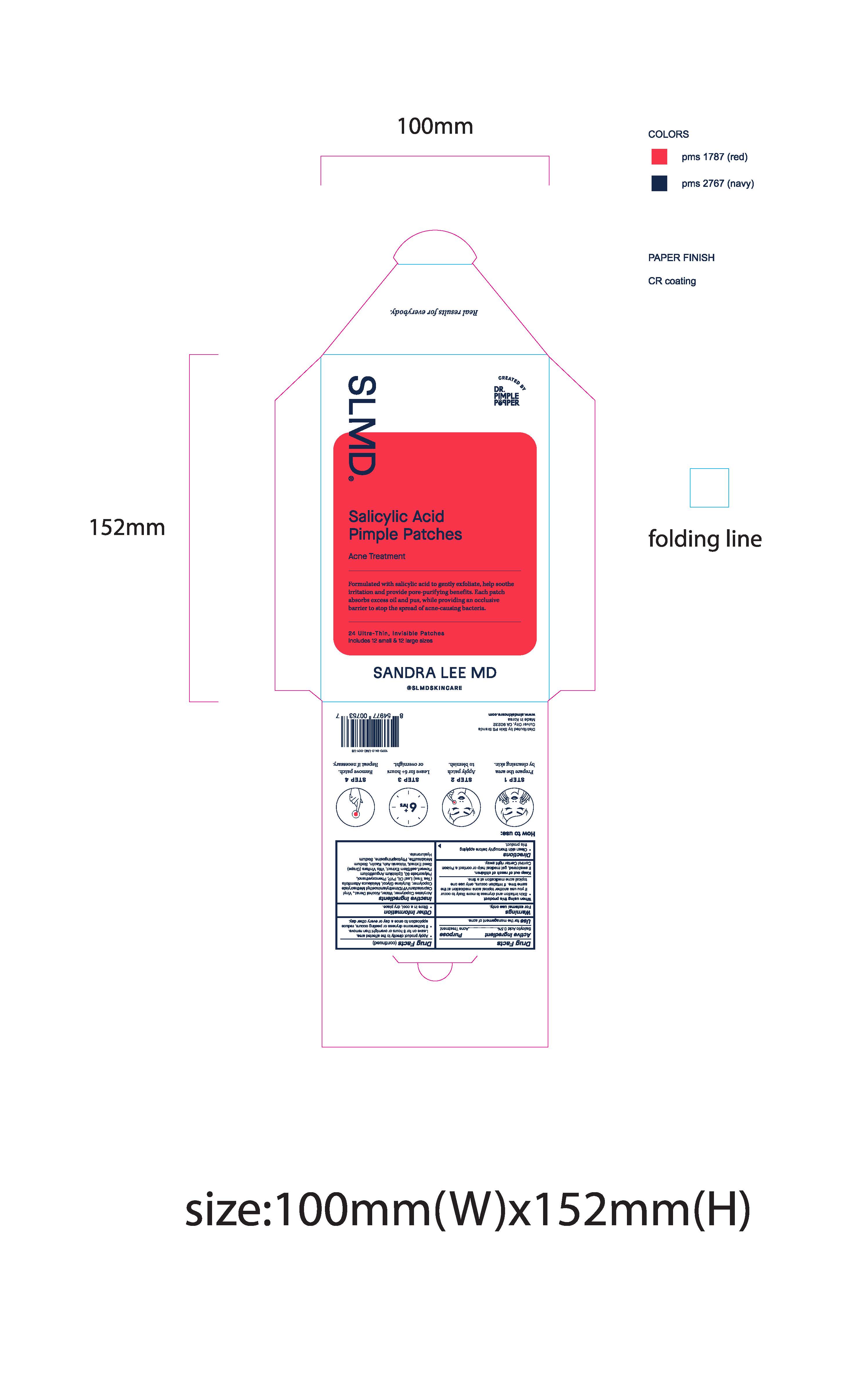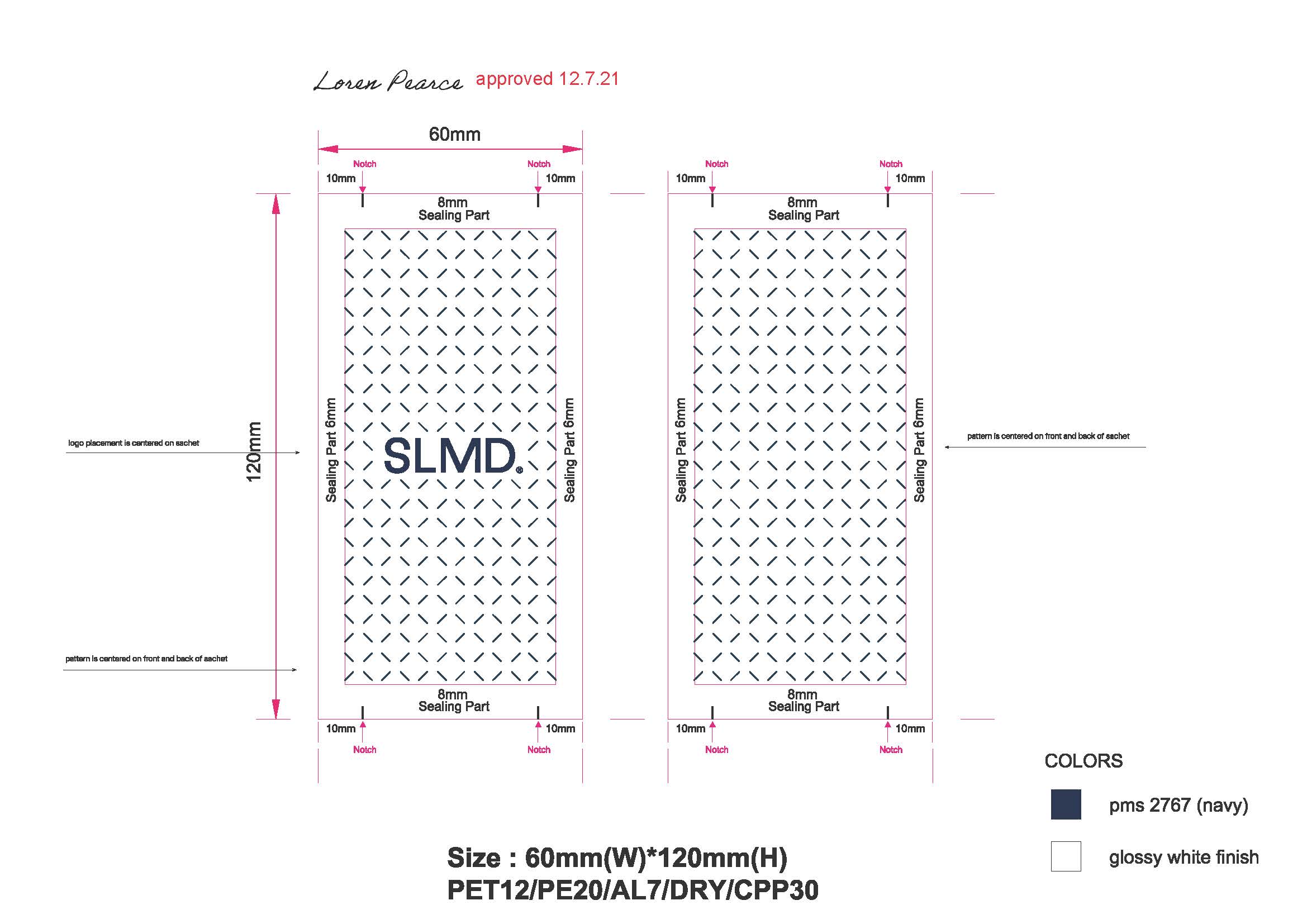 DRUG LABEL: Salicylic Acid Pimple Patches
NDC: 73318-1040 | Form: PATCH
Manufacturer: Skin PS Brands
Category: otc | Type: HUMAN OTC DRUG LABEL
Date: 20241227

ACTIVE INGREDIENTS: SALICYLIC ACID 5 mg/1 g
INACTIVE INGREDIENTS: KAOLIN; PHYTOSPHINGOSINE; ACRYLIC ACID/DIMETHICONE METHACRYLATE/ETHYLHEXYL ACRYLATE COPOLYMER; ALCOHOL; DIMETHYLAMINOETHYL METHACRYLATE - BUTYL METHACRYLATE - METHYL METHACRYLATE COPOLYMER; PHENOXYETHANOL; EPILOBIUM ANGUSTIFOLIUM WHOLE; SODIUM METABISULFITE; VITIS VINIFERA SEED; WATER; BUTYLENE GLYCOL; MELALEUCA ALTERNIFOLIA LEAF; POVIDONE K30; POLYSORBATE 80; HYALURONATE SODIUM

Salicylic Acid Pimple Patches

Active Ingredient

Salicylic Acid 0.5%

Purpose

Acne Treatment

Use

for the management of acne.

Warnings

For external use only.

When using this product

- Skin irritation and dryness is more likely to occur if you use another topical acne medication at the same time. If irritation occurs, only use one topical acne medication at a time.

Keep out of reach of children.

If swallowed, get medical help or contact a Poison Control Center right away.

Directions

- Clean skin thoroughly before applying this product
- Apply product directly to the affected area.
- Leave on for 6 hours or overnight then remove.
- If bothersome dryness or peeling occurs, reduce application to once a day or every other day.

Other Information

- Store in a cool, dry place

Inactive Ingredients

Acrylates Copolymer, Water, Alcohol Denat., Vinyl Caprolactam/VP/Dimethylaminoethyl, Methacrylate Copolymer, Butylene Glycol, Melaleuca Alternifolia (Tea Tree) Leaf Oil, PVP, Phenoxyethanol, Polysorbate 80, Epilobium Angustifolium Flower/Leaf/Stem Extract, Vitis Vinifera (Grape) Seed Extract, Volcanic Ash, Kaolin, Sodium Metabisulfite, Phytosphingosine, Sodium Hyaluronate.

How to use:

Step 1

Prepare the area by cleansing Skin

Step 2

Apply patch to blemish

Step 3

Leave for 6+ hours or overnight

Step 4

Remove patch. Repeat if necessary.

Questions or comments?

Distributed by Skin PS Brands

Culver City, CA 90232

Made in Korea

www.slmdskincare.com

SLMD Sandra Lee MD

Real results for everybody.

Created by Dr. Pimple Popper

SLMD

Salicylic Acid Pimple Patches

Acne Treatment

Formulated with salicylic acid to gently exfoliate, help soothe irritation and provide pore-purifying benefits. Each patch absorbs excess oil and pus, while providing an occlusive barrier to stop the spread of acne-causing bacteria.

24 Ultra-Thin, Invisible Patches

Includes 12 small & 12 large sizes

Pimple Patch Envelope:

Pimple Patch Sachet: